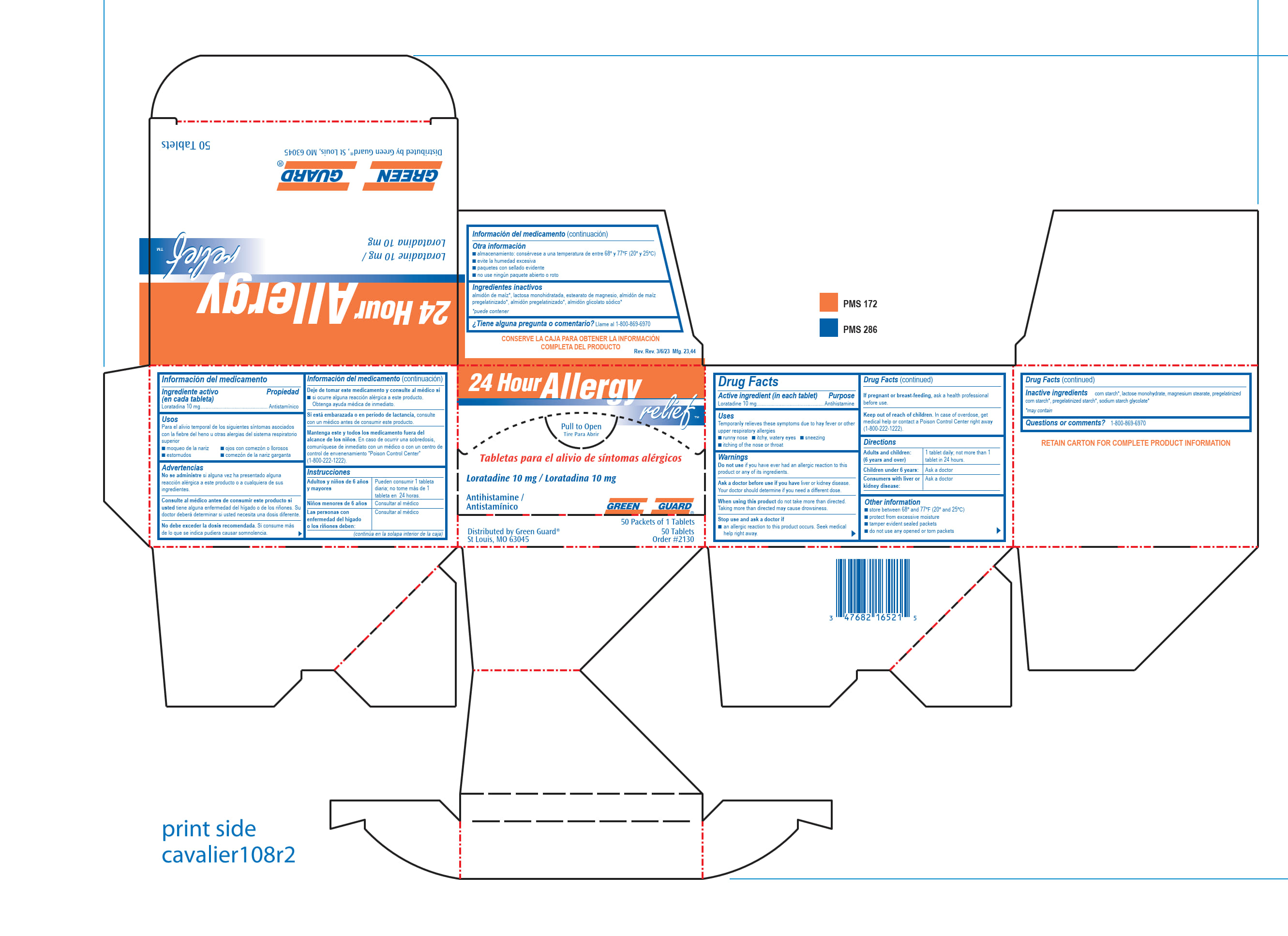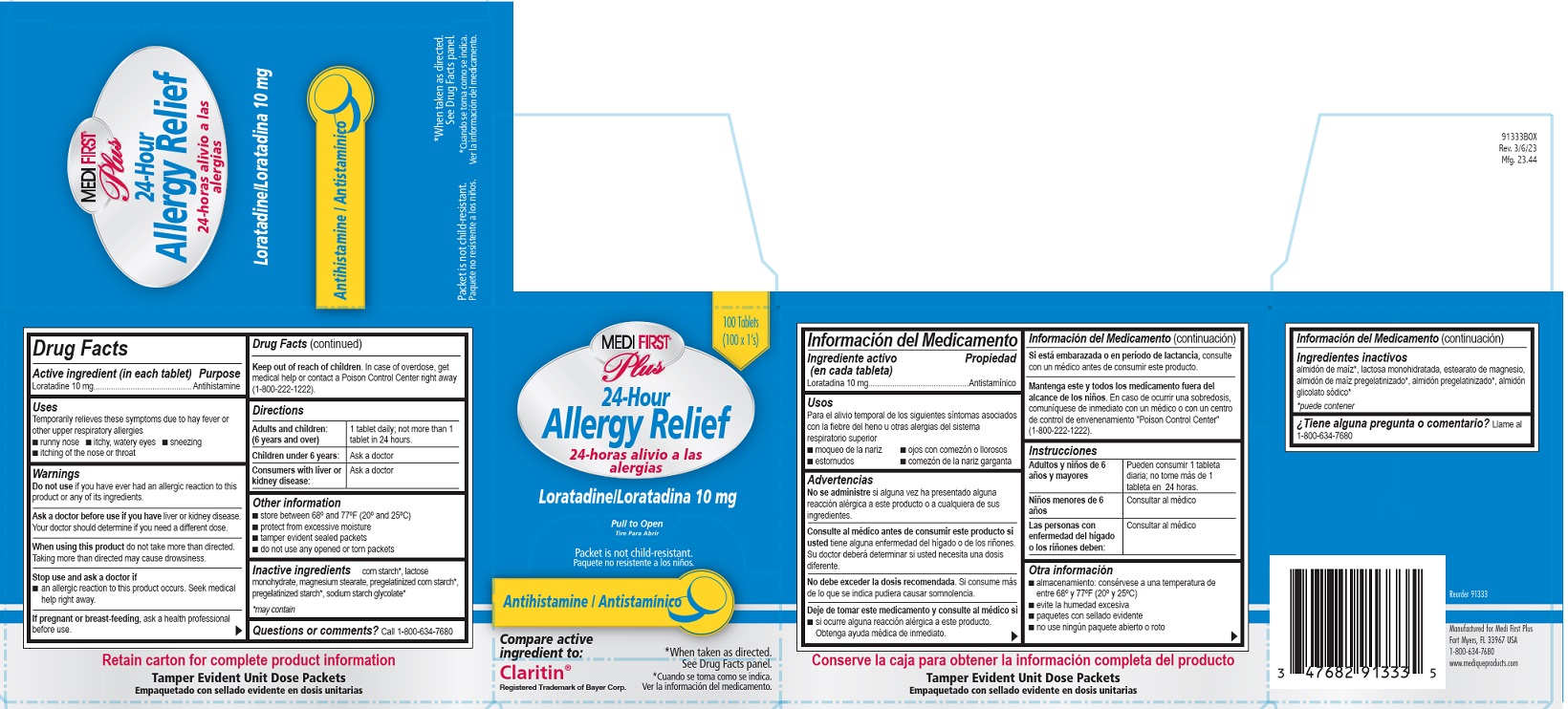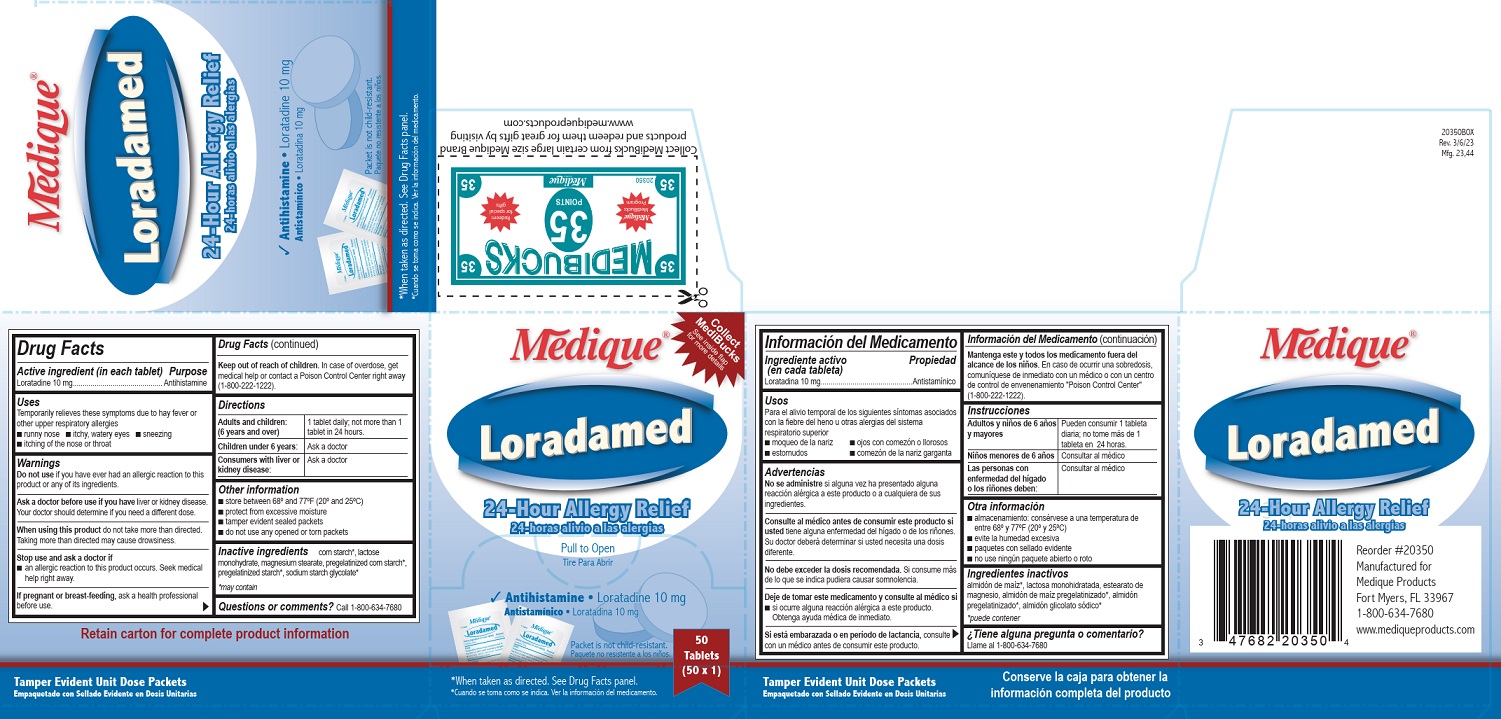 DRUG LABEL: Medi First Plus Allergy Relief
NDC: 47682-913 | Form: TABLET, FILM COATED
Manufacturer: Unifirst First Aid Corporation
Category: otc | Type: HUMAN OTC DRUG LABEL
Date: 20251121

ACTIVE INGREDIENTS: LORATADINE 10 mg/1 1
INACTIVE INGREDIENTS: LACTOSE MONOHYDRATE; MAGNESIUM STEARATE; STARCH, CORN

Medique Loradamed

Drug Facts

Active ingredient (in each tablet)

Loratadine 10 mg

Purpose

Antihistamine

Uses

Temporarily relieves these symptoms due to hay fever or other upper respiratory allergies

- runny nose
- itchy, watery eyes
- sneezing
- itching of the nose or throat

Warnings

Do not use if you have ever had an allergic reaction to this product or any of its ingredients.

Ask a doctor before use if you have liver or kidney disease.

Your doctor should determine if you need a different dose.

When using this product do not take more than directed.

Taking more than directed may cause drowsiness.

Stop use and ask a doctor if

- an allergic reaction to this product occurs. Seek medical help right away.

PREGNANCY OR BREAST FEEDING

If pregnant or breast-feeding, ask a health professional before use.

Keep out of reach of children. In case of overdose, get medical help or contact a Poison Control Center right away (1-800-222-1222).

Directions

Adults and children (6 years and over)

1 tablet daily, not more than 1 tablet in 24 hours.

Children under 6 years:

Ask a doctor

Consumer with liver or kidney disease:

Ask a doctor

Other information

- store between 68º and 77ºF (20º and 25ºC)
- protect from excessive moisture
- tamper evident sealed packets
- do not use any opened or torn packets

Inactive ingredients

corn starch*, lactose monohydrate, magnesium stearate, pregelatinized corn starch*, pregelatinized starch*, sodium starch glycolate*

* may contain

Questions or comments? Call 1-800-634-7680

Medique Loradamed Label

Medique®

Loradamed

Antihistamine • Laratadine 10 mg

Antistaminico • Loratadina 10 mg

24-Hour Allergy Relief

24-horas alivio a las alergias

Pull to Open

Tire Para Abrir

packet not child-resistant.

Paquete no resistente a los ninos

*When taken as directed. See Drug Facts panel.

*Cuando se toma coma se indica. Ver la informacion del medicamento.

Collect Medibucks

See inside flap for more details

50 Tablets (50 x 1)

Medi-First Plus Allergy Relief Label

Medi-First® Plus

24-Hour Allergy Relief

24-horas alivo a las alergias

Laratadine/ Loratadina 10 mg

Pull to Open

Tire Para Abrir

Antihistamine/Antistaminico

Packet is not child-resistant.

Paquete no resistente a los ninos.

*When taken as directed. See Drug Facts panel.

*Cuando se toma coma se indica. Ver la informacion del medicamento.

Compare active ingredient to:

Claritin®

Registered Trademark of Bayer Corp.

Green Guard 24 Hour Allergy Relief

24 Hour Allergy

Relief ™

Pull to Open

Tire Para Abrir

Tabletas para el alivio de síntomas alérgicos

Loratadine 10 mg / Loratadina 10 mg

Antihistamine /

Antistamínico

Green Guard

50 Packets of 1 Tablets

Distributed by Green Guard ®

50 tablets

St Louis, MO 63045

Order #2130